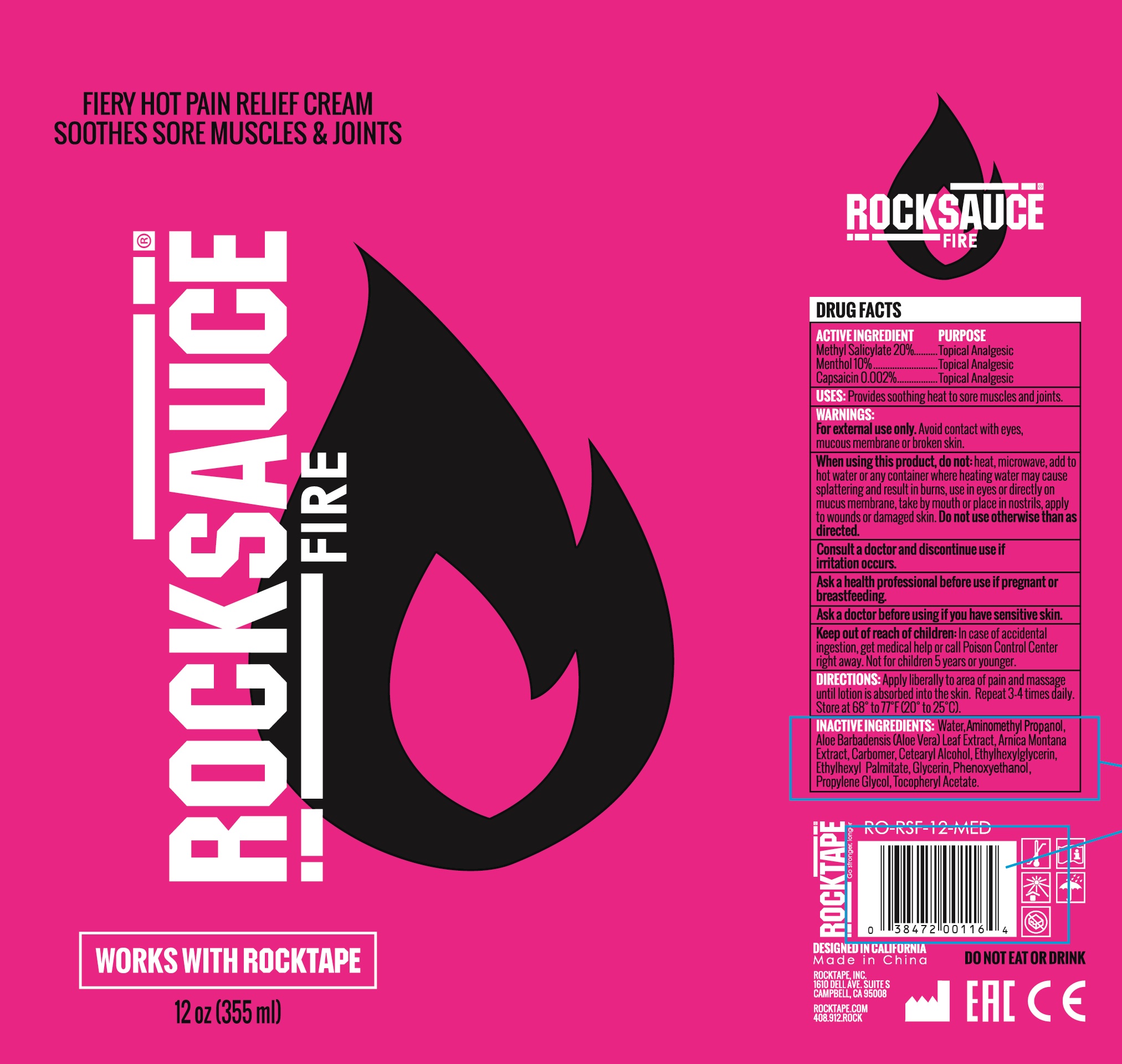 DRUG LABEL: rocksauce fire
NDC: 73344-103 | Form: CREAM
Manufacturer: NINGBO SANTE YING MEDICALAND HEALTHDEVELOPMENT CO.,LTD
Category: otc | Type: HUMAN OTC DRUG LABEL
Date: 20190929

ACTIVE INGREDIENTS: METHYL SALICYLATE 20 mg/100 mL; MENTHOL 10 mg/100 mL; CAPSAICIN 0.2 mg/100 mL
INACTIVE INGREDIENTS: ARNICA MONTANA; ETHYLHEXYL PALMITATE; GLYCERIN; ETHYLHEXYLGLYCERIN; PROPYLENE GLYCOL; METHYLISOTHIAZOLINONE; WATER

FIERY HOT PAIN RELIEF CREAM SOOTHES SORE MUSCLES AND JOINTS

Active ingredients

Methyl Salicylate 20%

Menthol USP 10%

Capsaicin 0.002%

Purpose

Topical Analgesic

Uses:

Provides soothing Cold to sore muscles and joints

Warnings:

For external use only.

Avoid contact with eyes, mucous membrane or broken skin

Keep out of reach of children.

if accidental ingestion, get medical help or call a Poison Control Center right away.

Directions:

Apply liberally to area of pain and massage unti lotion is absorbed into the skin. Repeat 3-4 times daily. Store at 68° to77°F (20°to 25°C).

When using this product

do not heat, microwave, and to hot water or any container where heating water may cause splattering and result in burns, use in eyes or directly on mucus membrans, take by mouth or place in nostrill, apply to wounds or damaged skin. Do not use otherwise than as directed

Consult a doctor and discontinus use.

if irritation occurs, ask a health professional before use if pregnant or brastfeeding. before using if you have sensitive skin.

Inactive ingredients:

Water, Aminomethyl Propanol, Aloe Barbadensis (Aloe Vera) Leaf Extract, Arnica Montana Extract, Carbomer, Cetearl Alcohol, Ethylhexylglycerin, Ethylhexyl Palmitate, Glycerin, Phenoxyethanol, Propylene Glycol, Tocopheryl Acetate